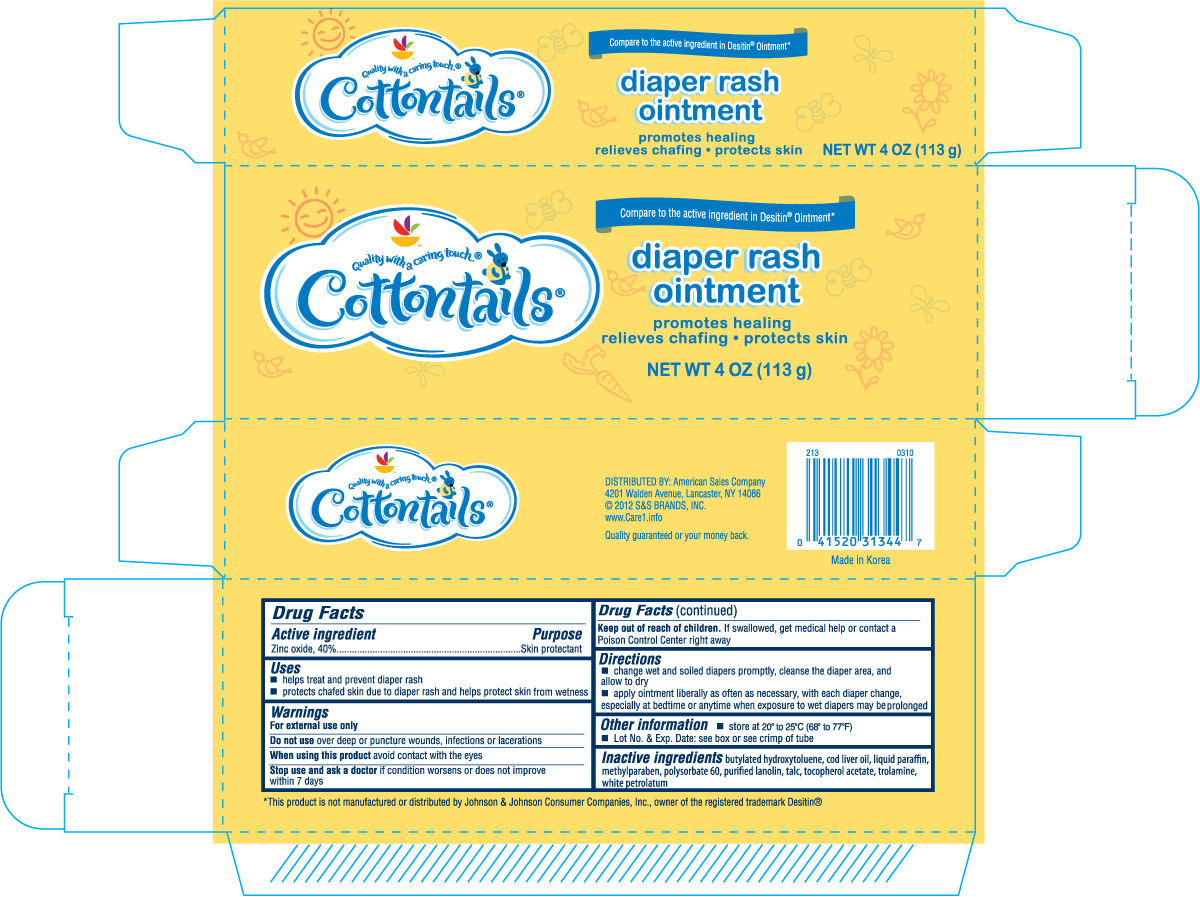 DRUG LABEL: COTTONTAILS DIAPER RASH
NDC: 41520-343 | Form: OINTMENT
Manufacturer: AMERICAN SALES
Category: otc | Type: HUMAN OTC DRUG LABEL
Date: 20120501

ACTIVE INGREDIENTS: ZINC OXIDE 0.4 g/1 g
INACTIVE INGREDIENTS: BUTYLATED HYDROXYTOLUENE; COD LIVER OIL; MINERAL OIL; METHYLPARABEN; POLYSORBATE 60; LANOLIN; TALC; PETROLATUM

Drug Facts

Active Ingredient Purpose

Zinc oxide, 40% .....................................................................Skin protectant

Uses

- helps treat and prevent diaper rash
- protects chafed skin due to diaper rash and helps protect skin from wetness

Warnings

For external use only

Do not use

over deep or puncture wounds, infections or lacerations

When using this product avoid contact with the eyes

Stop use and ask a doctor if condition worsens or does not improve within 7 days

Keep out of reach of children. If swallowed, get medical help or contact a Poison Control Center right away.

Directions

- change wet and soiled diapers promptly, cleanse the diaper area, and allow to dry
- apply ointment liberally as often as necessary, with each diaper change, especially at bedtime or anytime when exposure to wet diapers may be prolonged

Other information

- store at 20o to 25oC (68o to 77oF)
- Lot No. and Exp. Date: see box or see crimp of tube

Inactive ingredients

BHA, cod liver oil (high in vitamin A and D), fragrance, lanolin, methylparaben, petrolatum, talc and purified water, light mineral oil, tartrazine yellow #4 (FD and C yellow #4)

DOSAGE AND ADMINISTRATION

DISTRIBUTED BY: AMERICAN SALES COMPANY

4201 WALDEN AVENUE, LANCASTER, NY 14086

www.Care1.info

Made in Korea

PACKAGE LABEL

Enter section text here